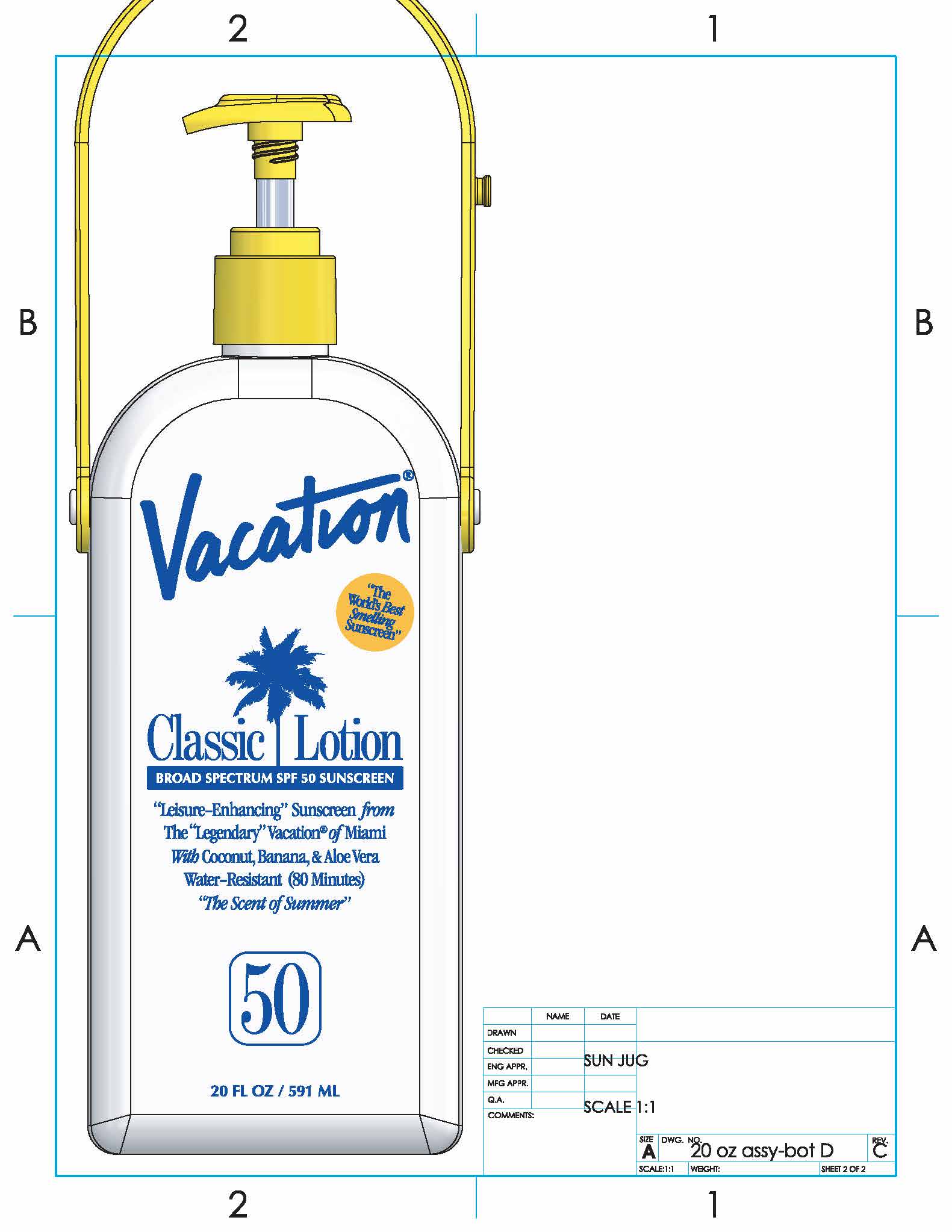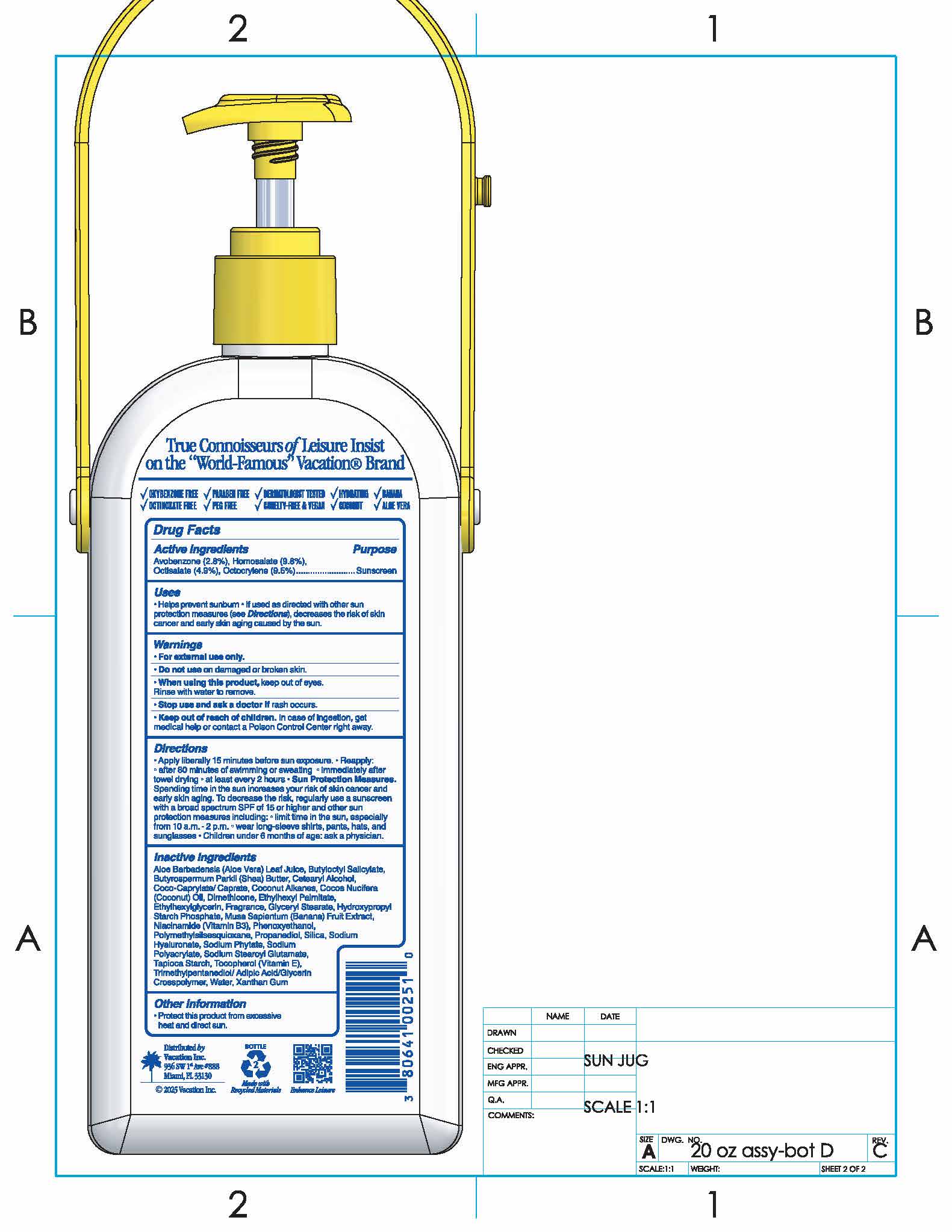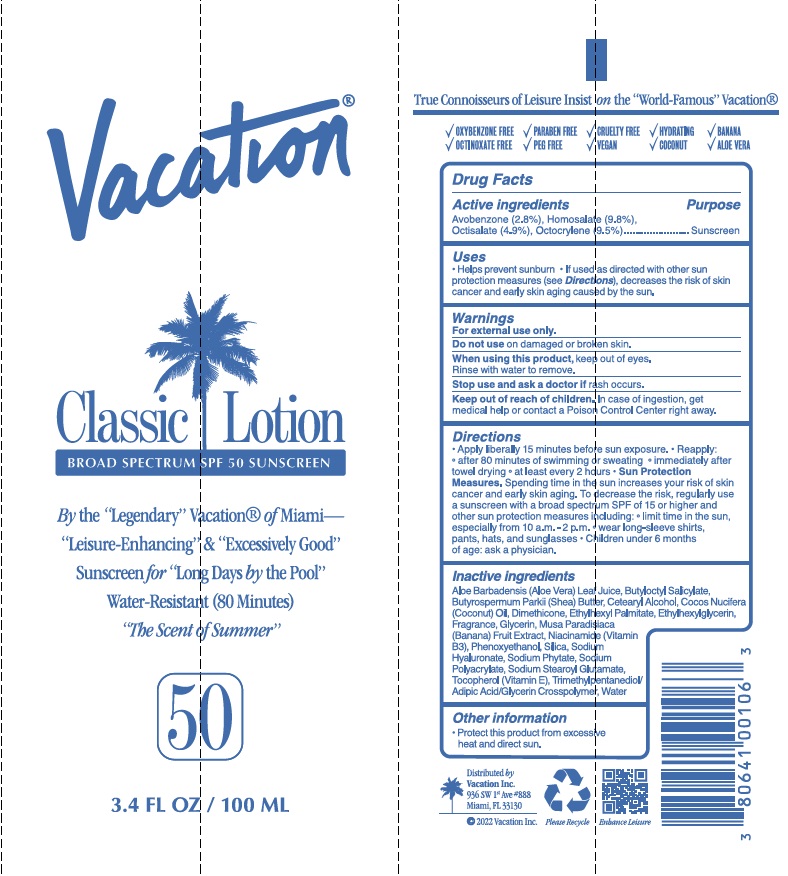 DRUG LABEL: Vacation SPF 50 Classic
NDC: 80641-006 | Form: LOTION
Manufacturer: Vacation Inc.
Category: otc | Type: HUMAN OTC DRUG LABEL
Date: 20250217

ACTIVE INGREDIENTS: OCTOCRYLENE 9.5 g/100 mL; AVOBENZONE 2.8 g/100 mL; HOMOSALATE 9.8 g/100 mL; OCTISALATE 4.9 g/100 mL
INACTIVE INGREDIENTS: BANANA; PHENOXYETHANOL; SODIUM STEAROYL GLUTAMATE; BUTYLOCTYL SALICYLATE; DIMETHICONE; HYALURONATE SODIUM; SILICON DIOXIDE; WATER; ALOE VERA LEAF; SHEA BUTTER; ETHYLHEXYL PALMITATE; PHYTATE SODIUM; GLYCERIN; COCONUT OIL; TOCOPHEROL; TRIMETHYLPENTANEDIOL/ADIPIC ACID/GLYCERIN CROSSPOLYMER (25000 MPA.S); ETHYLHEXYLGLYCERIN; SODIUM POLYACRYLATE (2500000 MW); NIACINAMIDE; CETOSTEARYL ALCOHOL

Vacation SPF 50 Classic Lotion

ACTIVE INGREDIENT

Avobenzone (2.%), Homosalate (9.8%), Octisalate (4.9%), Octocrylene (9.5%)

PURPOSE

Sunscreen

Uses

- Helps prevent sunburn
- If used as directed with other sun protection measures (see Directions), decreases the risk of skin cancer and early skin aging caused by the sun

WARNINGS

- For external use only
- Do not use on damaged or broken skin
- When using this product, keep out of eyes. Rinse with water to remove.
- Stop useand ask a doctor if rash occurs

Keep out of reach of children. In case of ingestion, get medical help or contact a Poison Control Center right away.

Directions

- Apply liberally 15 minutes before sun exposure.
- Reapply: after 80 minutes of swimming or sweating, immediately after towel drying, at least every 2 hours
- Sun Protection Measures. Spending time in the sun increases your risk of skin cancer and early skin aging. To decrease the risk, regularly use a sunscreen with a broad spectrum SPF of 15 or higher and other sun protection measures including: limit time in the sun, especially from 10 a.m. - 2 p.m., wear long-sleeve shirts, pants, hats, and sunglasses
- Children under 6 months of age: ask a physician.

INACTIVE INGREDIENT

Aloe Barbadensis (Aloe Vera) Leaf Juice, Butyloctyl Salicylate, Butyrospermum Parkii (Shea) Butter, Cetearyl Alcohol, Cocos Nucifera (Coconut) Oil, Dimethicone, Ethylhexyl Palmitate, Ethylhexylglycerin, Fragrance, Glycerin, Musa Paradisiaca (Banana) Fruit Extract, Niacinamide, Phenoxyethanol, Silica, Sodium Hyaluronate, Sodium Phytate, Sodium Polyacrylate, Sodium Stearoyl Glutamate, Tocopherol (Vitamin E), Trimethylpentanediol/Adipic Acid/Glycerin Crosspolymer, Water

Other Information

Protect this product from excessive heat and direct sun